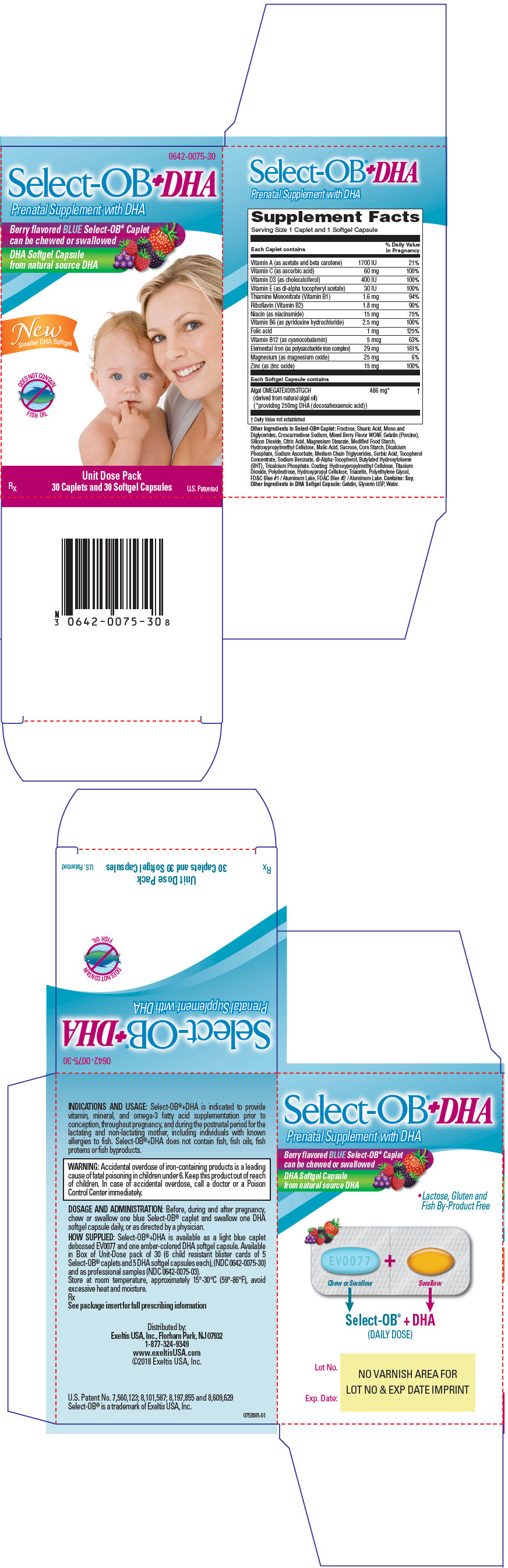 DRUG LABEL: Select-OB Plus DHA
NDC: 0642-0075 | Form: KIT | Route: ORAL
Manufacturer: Exeltis USA, Inc.
Category: prescription | Type: HUMAN PRESCRIPTION DRUG LABEL
Date: 20230724

ACTIVE INGREDIENTS: BETA CAROTENE 600 [iU]/1 1; VITAMIN A ACETATE 1100 [iU]/1 1; ASCORBIC ACID 60 mg/1 1; CHOLECALCIFEROL 400 [iU]/1 1; .ALPHA.-TOCOPHEROL ACETATE, DL- 30 [iU]/1 1; THIAMINE MONONITRATE 1.6 mg/1 1; RIBOFLAVIN 1.8 mg/1 1; NIACINAMIDE 15 mg/1 1; PYRIDOXINE HYDROCHLORIDE 2.5 mg/1 1; FOLIC ACID 0.4 mg/1 1; LEVOMEFOLATE CALCIUM 0.6 mg/1 1; COBALAMIN 5 ug/1 1; IRON 29 mg/1 1; MAGNESIUM OXIDE 25 mg/1 1; ZINC OXIDE 15 mg/1 1; DOCONEXENT 250 mg/1 1
INACTIVE INGREDIENTS: FRUCTOSE; STEARIC ACID; CROSCARMELLOSE SODIUM; DIACETYLTARTARIC AND FATTY ACID ESTERS OF GLYCEROL; SILICON DIOXIDE; CITRIC ACID MONOHYDRATE; TITANIUM DIOXIDE; GELATIN, UNSPECIFIED; MAGNESIUM STEARATE; MALIC ACID; HYDROXYPROPYL CELLULOSE (1600000 WAMW); TRIACETIN; STARCH, CORN; SUCROSE; MODIFIED CORN STARCH (1-OCTENYL SUCCINIC ANHYDRIDE); HYPROMELLOSE, UNSPECIFIED; ANHYDROUS DIBASIC CALCIUM PHOSPHATE; FD&C BLUE NO. 1; FD&C BLUE NO. 2; SODIUM ASCORBATE; MEDIUM-CHAIN TRIGLYCERIDES; SORBIC ACID; TOCOPHEROL; SODIUM BENZOATE; .ALPHA.-TOCOPHEROL, DL-; BUTYLATED HYDROXYTOLUENE; TRICALCIUM PHOSPHATE; POLYDEXTROSE; POLYETHYLENE GLYCOL, UNSPECIFIED; GLYCERIN; GELATIN, UNSPECIFIED; WATER

Select-OB+DHA®

0642-0075-30

Prenatal Supplement with DHA

Rx

COMPOSITION

Each SELECT-OB ® caplet contains:
Vitamin A (as retinyl acetate & beta carotene) | 510 mcg RAE (1700 IU)
Vitamin C (as ascorbic acid) | 60 mg
Vitamin D (as cholecalciferol) | 10 mcg (400 IU)
Vitamin E (as dl-alpha tocopheryl acetate) | 13.5 mg (30 IU)
Thiamin (Vitamin B1 as thiamine mononitrate) | 1.6 mg
Riboflavin (Vitamin B2) | 1.8 mg
Niacin (as niacinamide) | 15 mg NE
Vitamin B6 (as pyridoxine hydrochloride) | 2.5 mg
Folate (as folic acid) | 1700 mcg DFE
Vitamin B12 (as cyanocobalamin) | 5 mcg
Iron (as polysaccharide iron complex) | 29 mg
Magnesium (as magnesium oxide) | 25 mg
Zinc (as zinc oxide) | 15 mg
Each softgel capsule contains: Docosahexaenoic acid (DHA); (from natural algal oil) | 250 mg

Other Ingredients in Select-OB ® caplet: Fructose, Stearic Acid, Mono and Diglycerides, Croscarmellose Sodium, Mixed Berry Flavor WONF, Gelatin (Porcine), Silicon Dioxide, Citric Acid, Magnesium Stearate, Modified Food Starch, Hydroxypropylmethyl Cellulose, Malic Acid, Sucrose, Corn Starch, Dicalcium Phosphate, Sodium Ascorbate, Medium Chain Triglycerides, Sorbic Acid, Tocopherol Concentrate, Sodium Benzoate, dl-Alpha-Tocopherol, Butylated Hydroxytoluene (BHT), Tricalcium Phosphate. Coating: Hydroxypropylmethyl Cellulose, Titanium Dioxide, Polydextrose, Hydroxypropyl Cellulose, Triacetin, Polyethylene Glycol, FD&C Blue #1 / Aluminum Lake, FD&C Blue #2 / Aluminum Lake. Contains: Soy

Other Ingredients in DHA softgel capsule: Gelatin, Glycerin USP, Water.

INDICATIONS AND USAGE

Select-OB+DHA® is indicated to provide vitamin, mineral, and omega-3 fatty acid supplementation prior to conception, throughout pregnancy, and during the postnatal period for the lactating and non-lactating mother.*

Select-OB+DHA® does not contain fish, fish oils, fish proteins or fish byproducts.

CONTRAINDICATIONS

Select-OB+DHA® is contraindicated in patients with hypersensitivity to any of its components or color additives. Folic acid is contraindicated in patients with untreated and uncomplicated pernicious anemia, and in those with anaphylactic sensitivity to folic acid. Iron therapy is contraindicated in patients with hemochromatosis and patients with iron storage disease or the potential for iron storage disease due to chronic hemolytic anemia (e.g., inherited anomalies of hemoglobin structure or synthesis and/or red cell enzyme deficiencies, etc.), pyridoxine responsive anemia, or cirrhosis of the liver.

Cyanocobalamin is contraindicated in patients with sensitivity to cobalt or to cyanocobalamin (vitaminB12).

WARNING

Accidental overdose of iron-containing products is a leading cause of fatal poisoning in children under 6. Keep this product out of reach of children. In case of accidental overdose, call a doctor or a Poison Control Center immediately.

WARNINGS/PRECAUTIONS

Select-OB+DHA® should be used with caution in patients with known sensitivity or allergy to soy.

Vitamin D supplementation should be used with caution in those with hypercalcemia or conditions that may lead to hypercalcemia such as hyperparathyroidism and those who form calcium-containing kidney stones. High doses of vitamin D can lead to elevated levels of calcium that reside in the blood and soft tissues. Bone pain, high blood pressure, formation of kidney stones, renal failure, and increased rick of heart disease can occur. Prolonged use of iron slats may produce iron storage disease.

Folic acid, especially in doses above 0.1 mg daily, may obscure pernicious anemia, in that hematologic remission may occur while neurological manifestations remain progressive. The use of folic acid doses above 1 mg daily may precipitate or exacerbate the neurological damage of vitamin B12 deficiency. Consumption of more than 3 grams of omega-3 fatty acids per day from all sources may lead to excessive bleeding.

Supplemental intake of omega-3 fatty acids such as DHA exceeding 2 grams per day is not recommended.

Avoid overdosage. Keep out of the reach of children.

Drug Interactions

High doses of folic acid may result in decreased serum levels of the anticonvulsant drugs.

Vitamin D supplementation should not be given with large amounts of calcium in those with hypercalcemia or conditions that may lead to hypercalcemia such as hyperparathyroidism and those who form calcium-containing kidney stones.

Zinc can inhibit the absorption of certain antibiotics; take at least 2 hours apart to minimize interactions. Consult appropriate references for additional specific vitamin-drug interactions.

Information for Patients

Patients should be counseled to disclose all medical conditions, including use of all medications, vitamins and supplements, pregnancy, and breast-feeding.

Pediatric Use

Not for pediatric use.

ADVERSE REACTIONS

Adverse reactions have been reported with specific vitamins and minerals, but generally at doses substantially higher than those in Select-OB+DHA®.

DOSAGE AND ADMINISTRATION

Before, during and after pregnancy, chew or swallow one blue Select OB® caplet and swallow one DHA softgel capsule daily, or as directed by a physician.

HOW SUPPLIED

Select-OB+DHA® is available as a light blue caplet debossed EV0077 and one amber-colored DHA softgel capsule. Available in Box of Unit-Dose pack of 30 (5 child resistant blister cards of 6 SELECT-OB® caplets and 6 DHA softgel capsules each) (0642-0075-30) and as professional samples (0642-0075-03).

STORAGE AND HANDLING

Store at room temperature, approximately 15°-30°C (59°-86°F), avoid excessive heat and moisture.

*These statements have not been evaluated by the Food and Drug Administration.This product is not intended to diagnose, treat, cure, or prevent any disease.

Rx

Distributed by:
Exeltis USA, Inc.
Florham Park, NJ 07932
1-877-324-9349
www.exeltisusa.com
©2023 Exeltis USA, Inc. All rights reserved.

U.S. Patent No. 7,560,123; 8,101,587; 8,197,855; and 8,609,629
Select-OB+DHA® is a trademark of Exeltis Healthcare, S.L.

Rev. January 2023 0753001-02

PRINCIPAL DISPLAY PANEL - Kit Carton

0642-0075-30

Select-OB+DHA®
Prenatal Supplement with DHA

Berry flavored BLUE Select-OB® Caplet
can be chewed or swallowed

DHA Softgel Capsule
from natural source DHA

Smaller DHA Softgel

DOES NOT CONTAIN
FISH OIL

RX
Unit Dose Pack
30 Caplets and 30 Softgel Capsules
U.S. Patented